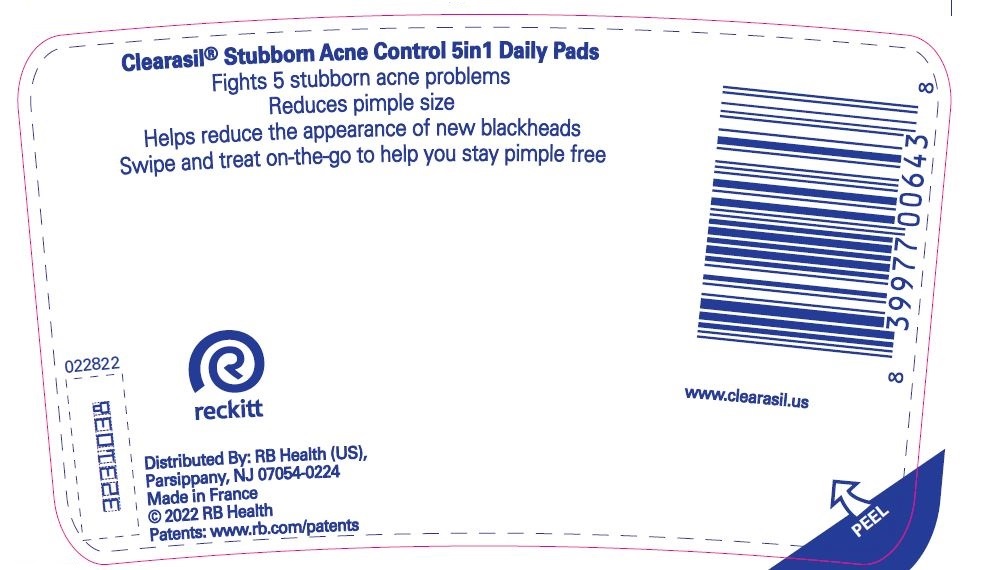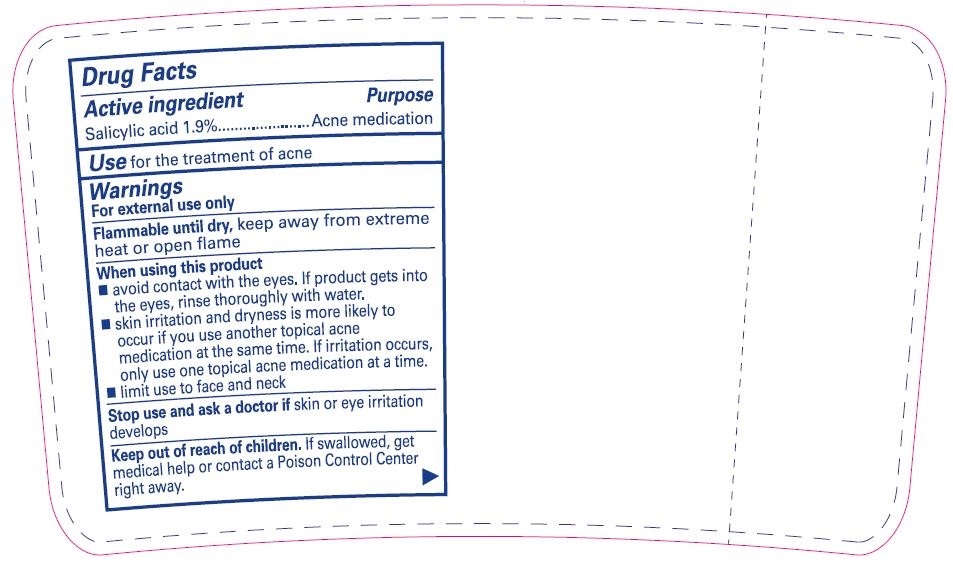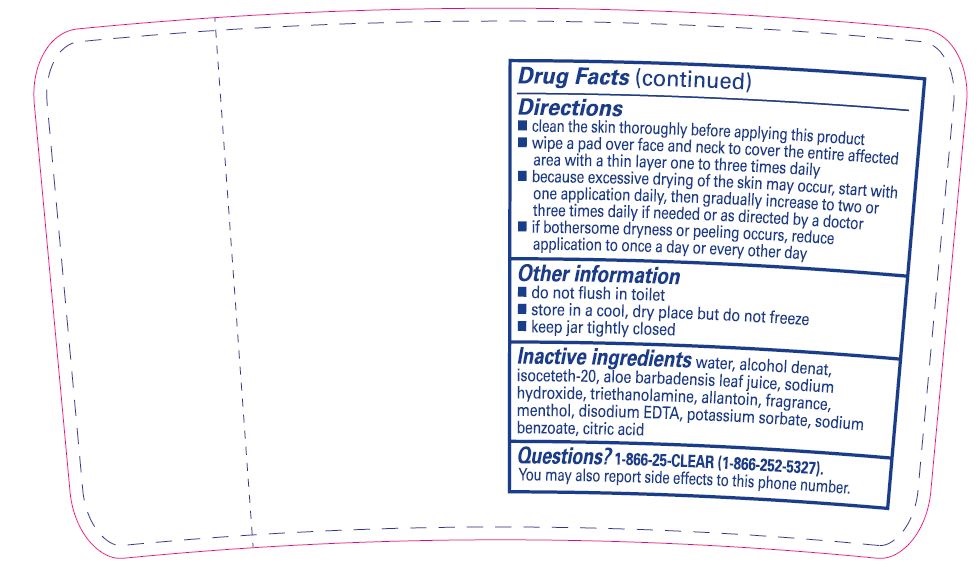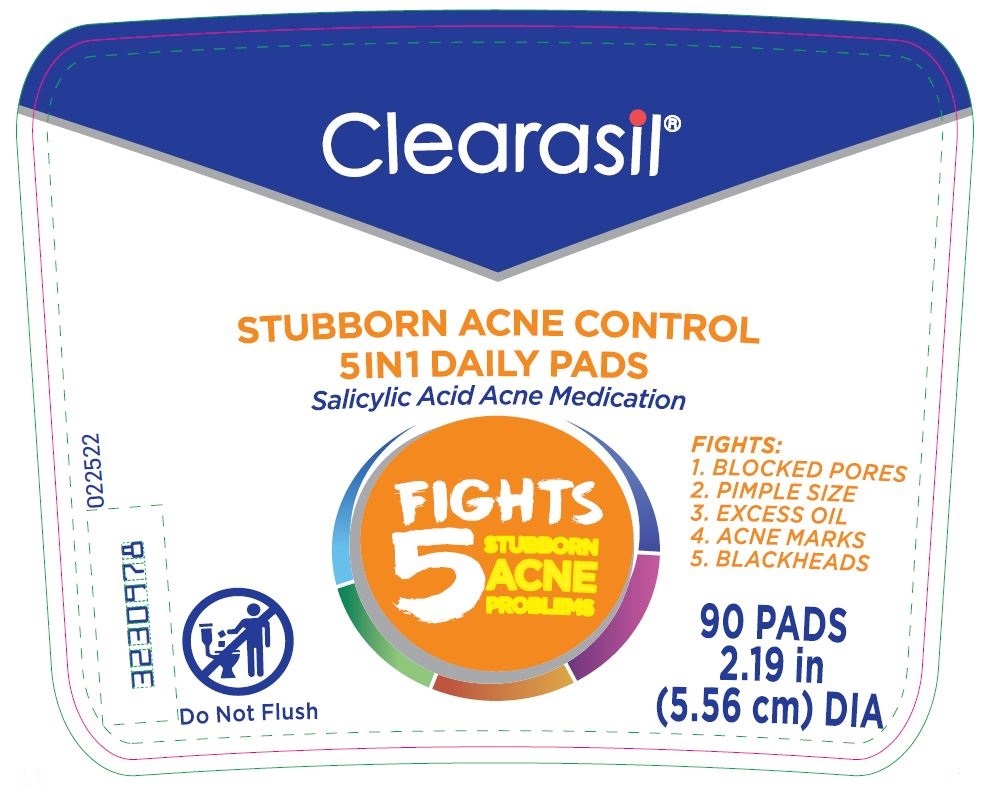 DRUG LABEL: Clearasil Stubborn Acne Control 5in1 Daily Pads
NDC: 63824-439 | Form: CLOTH
Manufacturer: RB Health (US) LLC
Category: otc | Type: HUMAN OTC DRUG LABEL
Date: 20241218

ACTIVE INGREDIENTS: SALICYLIC ACID 0.03 g/1 1
INACTIVE INGREDIENTS: WATER; ALCOHOL; ISOCETETH-20; ALOE VERA LEAF; SODIUM HYDROXIDE; TROLAMINE; ALLANTOIN; MENTHOL, UNSPECIFIED FORM; EDETATE DISODIUM ANHYDROUS; POTASSIUM SORBATE; SODIUM BENZOATE; CITRIC ACID MONOHYDRATE

Clearasil®Stubborn Acne Control 5in1 Daily Pads

Drug Facts

Active ingredient

Salicylic acid 1.9%

Purpose

Acne medication

Use

for the treatment of acne

Warnings

For external use only

Flammable until dry,keep away from extreme heat or open flame

When using this product

- avoid contact with the eyes. If product gets into the eyes rinse thoroughly with water.
- skin irritation and dryness is more likely to occur if you use another topical acne medication at the same time. If irritation occurs, only use one topical acne medication at a time.
- limit use to face and neck

Stop use and ask a doctor ifskin or eye irritation develops

Keep out of reach of children.If swallowed, get medical help or contact a Poison Control Center right away.

Directions

- clean the skin thoroughly before applying this product
- wipe a pad over face and neck to cover the entire affected area with a thin layer one to three times daily
- because excessive drying of the skin may occur, start with one application daily, then gradually increase to two or three times daily if needed or as directed by a doctor
- if bothersome dryness or peeling occurs, reduce application to once a day or every other day

Other information

- do not flush in toilet
- store in a cool, dry place but do not freeze
- keep jar tightly closed

Inactive ingredients

Water, Alcohol Denat, Isoceteth-20, Aloe Barbadensis Leaf Juice, Sodium Hydroxide, Triethanolamine, Allantoin, Fragrance, Menthol, Disodium EDTA, Potassium Sorbate, Sodium Benzoate, Citric Acid

Questions?

Call 1-866-25-CLEAR (1-866-252-5327).

You may also report side effects to this phone number.

Distributed By: RB Health (US),
Parsippany, NJ 07054-0224
Made in France

PRINCIPAL DISPLAY PANEL - 90 Pad Jar Label

Clearasil®

STUBBORN ACNE CONTROL
5IN1 DAILY PADS

Salicylic Acid Acne Medication

FIGHTS
5
STUBBORN
ACNE
PROBLEMS

FIGHTS:
1. BLOCKED PORES
2. PIMPLE SIZE
3. EXCESS OIL
4. ACNE MARKS
5. BLACKHEADS

90 PADS
2.19 in
(5.56 cm) DIA

082117